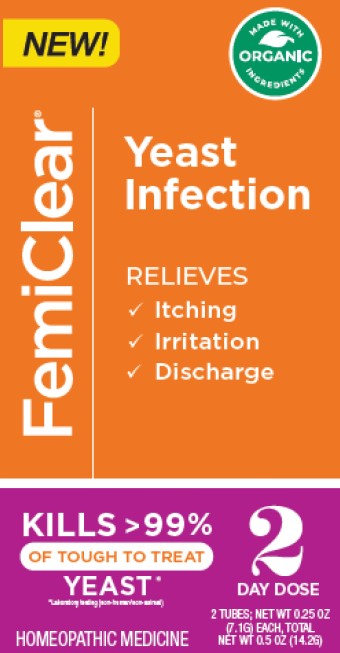 DRUG LABEL: FemiClear Yeast Infection
NDC: 71042-026 | Form: OINTMENT
Manufacturer: OrganiCare Nature's Science, LLC
Category: homeopathic | Type: HUMAN OTC DRUG LABEL
Date: 20251020

ACTIVE INGREDIENTS: CAJUPUT OIL 0.1 kg/1 kg; CALENDULA OFFICINALIS WHOLE 1 kg/1 kg
INACTIVE INGREDIENTS: PEAR; YELLOW WAX; OLIVE OIL

FemiClear 2 Day Simple

Active Ingredients

Calendula 2X HPUS

Melaleuca 3X HPUS

Olive Extract 3X HPUS

Purpose

Healing agent

Anti-yeast agent

Anti-microbial and healing agent

Uses

Treats vaginal yeast infections

Warnings

For vaginal use only.

FemiClear may damage condoms and diaphragms and cause them to fail

Ask a doctor before use if you have:

vaginal itching and discomfort for the first time

lower abdomen, back or shoulder pain, fever fever, chills, nausea, vomiting or foul-smelling vaginal discharge. You may have a more serious condition.

vaginal yeast infections often (such as once a month or 3 in 6 months). You could be pregnant or have a serious underlying medical cause for your symptoms, including diabetes or a weakened immune system.

been exposed to the human immunodeficiency virus (HIV) that causes AIDS

Do not use

if you are allergic to any ingredient in this product

When using this product

do not use tampons, douches, spermicides or other vaginal products. Condoms and diaphragms may be damaged and fail to prevent pregnancy or sexually transmitted infections (STIs)

do not have vaginal intercourse

mild increase in vaginal burning, itching, or irritation may occur

if you do not get complete relief, ask a doctor before using another product

Stop use and ask a doctor if

symproms do not get better in 3 days

symptoms last more than 7 days

you get a rash or hives, abdominal pain, fever, chills, nausea, vomiting or foul-smelling discharge

If pregnant or breastfeeding

ask a healthcare professional before use.

Keep out of the reach of children.

If swallowed, get medical help or contact a Poison Control Center right away.

Directions

Adults and children 12 years or over:

Vaginal Ointment: use at bed time, read enclosed instructions for complete directions.

to protect clothes, use panty liner.

fill applicator with Vaginal Ointment - use one of the tubes

lie down in bed. Insert applicator into vagina and inject FemiClear. Remain laying down to avoid leakage.

discard applicator after use. DO NOT reuse.

repeat on second night - use other tube.

Children under 12 years: ask a doctor.

Other information

do not use if applicator wrapper is torn, open or incompletely sealed

do not use if seal over tube opening has been punctured

Other Information

Store at 68-77 F (20 C - 25 C)

If liquified, refrigerate 10 minutes to thicken.

Inactive ingredients

beeswax, essential oil (natural fragrance), oxygenated olive oil

Questions?

Call 512.401.3572 or vist femiclear.com. OrganiCare, LLC, Austin TX 78744, USA

Made and Distributed by

OrganiCare

Austin, TX 78744 USA

PACKAGE LABEL

FemiClear

Yeast Infection

Relieves

Itching

Irritation

Discharge

Kills >99%

of tough to treat

yeast*

*Laboratory testing (non-human/non-animal)

Homeopathic Medicine

2 Day Dose

2 Tubes; Net Wt 0.25 oz

(7.1G) each, Total Net Wt 0.5 oz (14.2G)